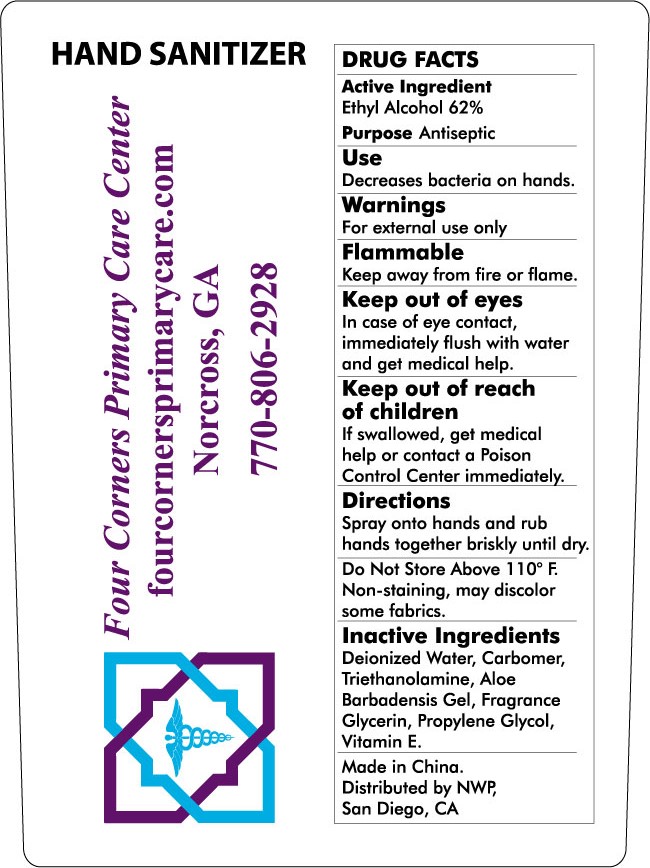 DRUG LABEL: Hand Sanitizer
NDC: 58004-002 | Form: SPRAY
Manufacturer: NATIONWIDE PROMOTIONS LLC
Category: otc | Type: HUMAN OTC DRUG LABEL
Date: 20130501

ACTIVE INGREDIENTS: ALCOHOL 62 mL/100 mL
INACTIVE INGREDIENTS: WATER; CARBOMER COPOLYMER TYPE A (ALLYL PENTAERYTHRITOL CROSSLINKED); TROLAMINE; ALOE VERA LEAF; GLYCERIN; PROPYLENE GLYCOL; .ALPHA.-TOCOPHEROL

Drug Facts

Active Ingredient

Ethyl Alcohol 62%

Purpose

Antiseptic

Keep Out of Reach of Children

If swallowed, get medical help or contact a Poison on Control Center immediately

Use

Decreases bacteria on hands

Warnings

For external use only
Flammable Keep away from fire or flame
Keep out of eyes In case of eye contact immediaterly flush with water and get medical help

Dosage and Administration

Spray on to hands and rub hands together briskly until dry

Inactive Ingredients

Deionized Water, Carbomer ,Triethanolamine, Aloe barbadensis Gel, Fragrance Glycerin,
Propylene Glycol,Vitamin E